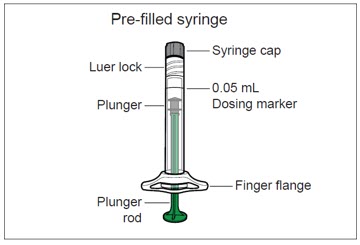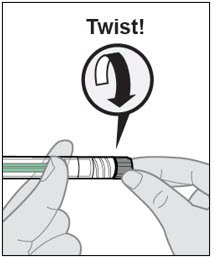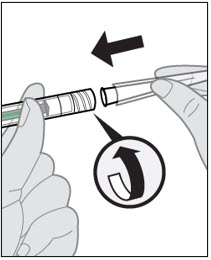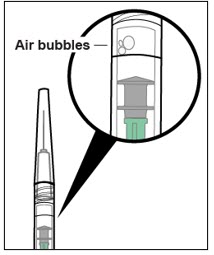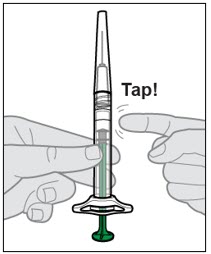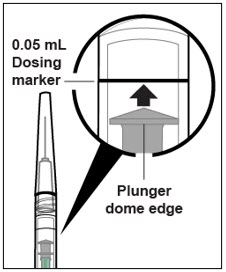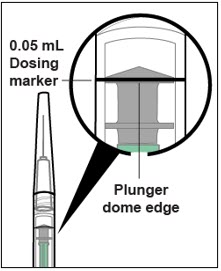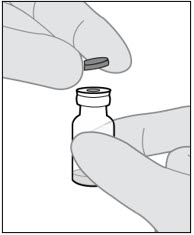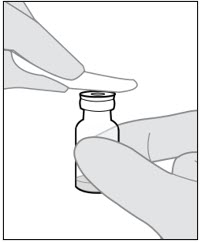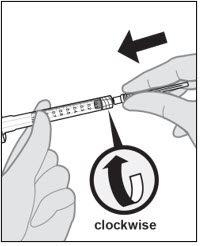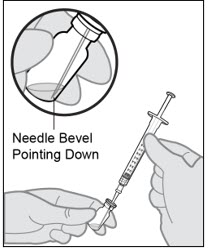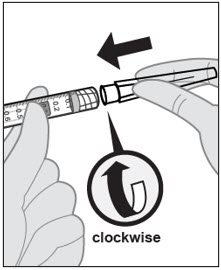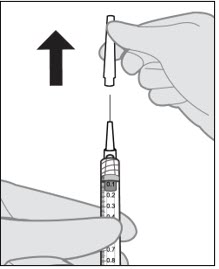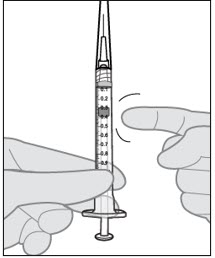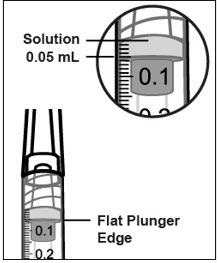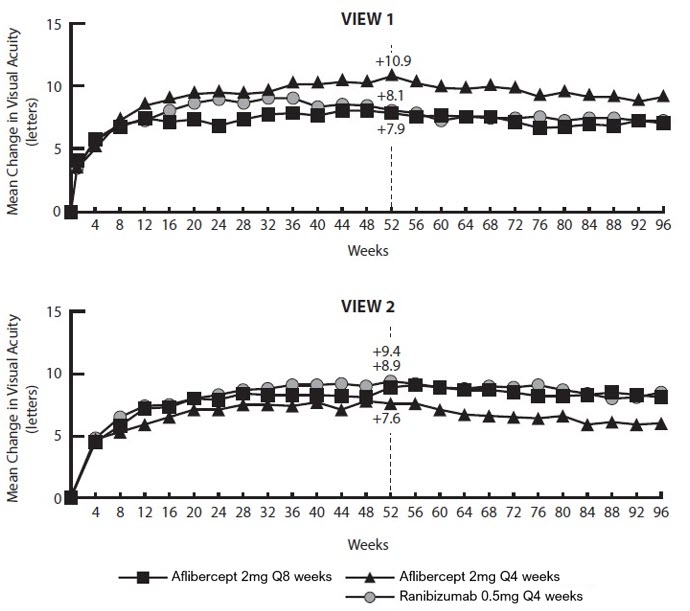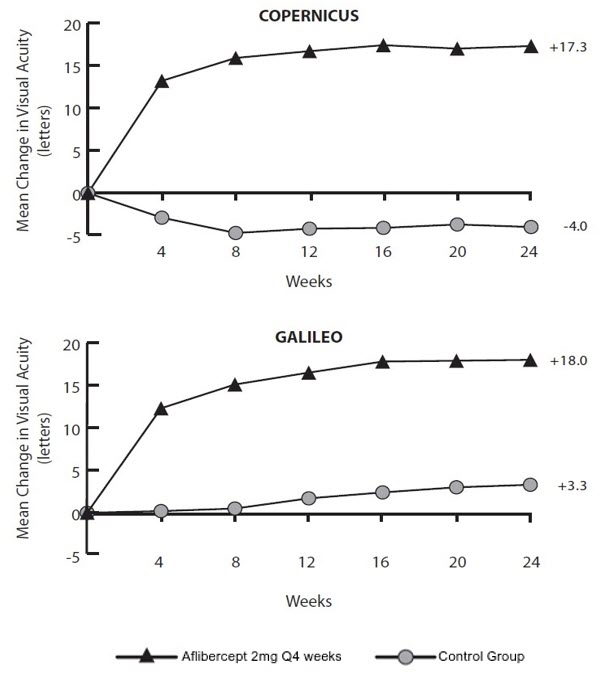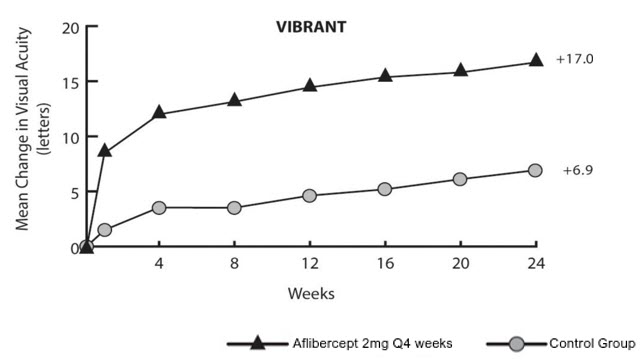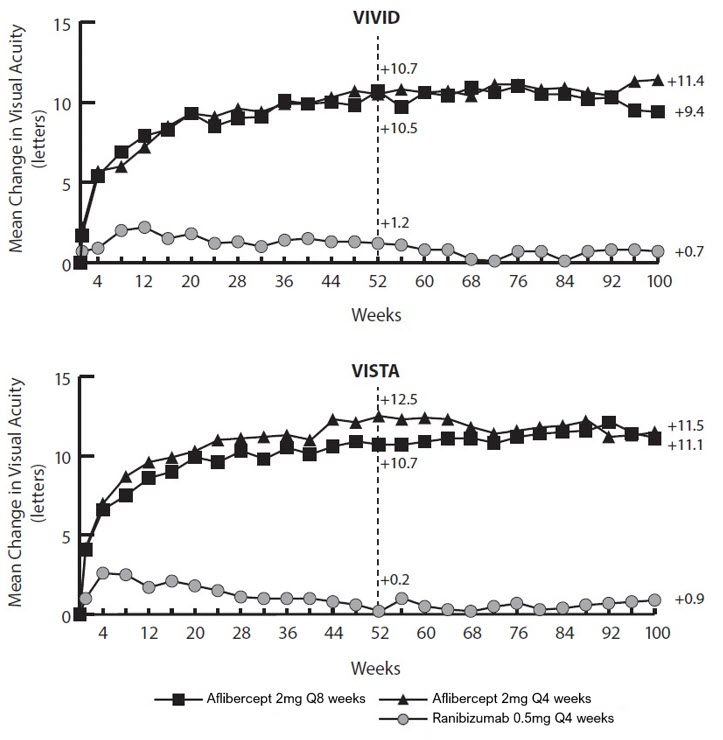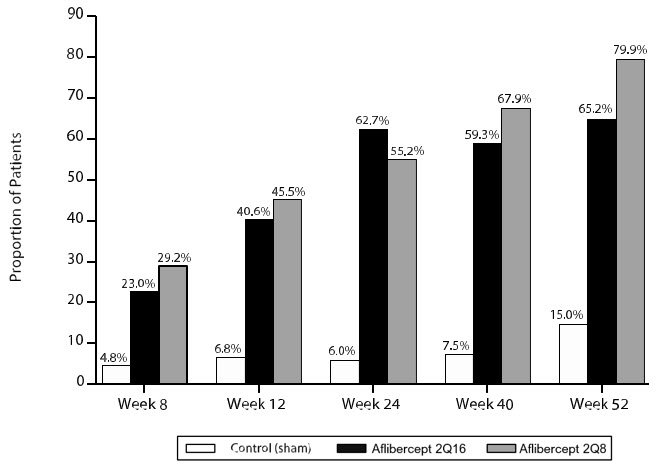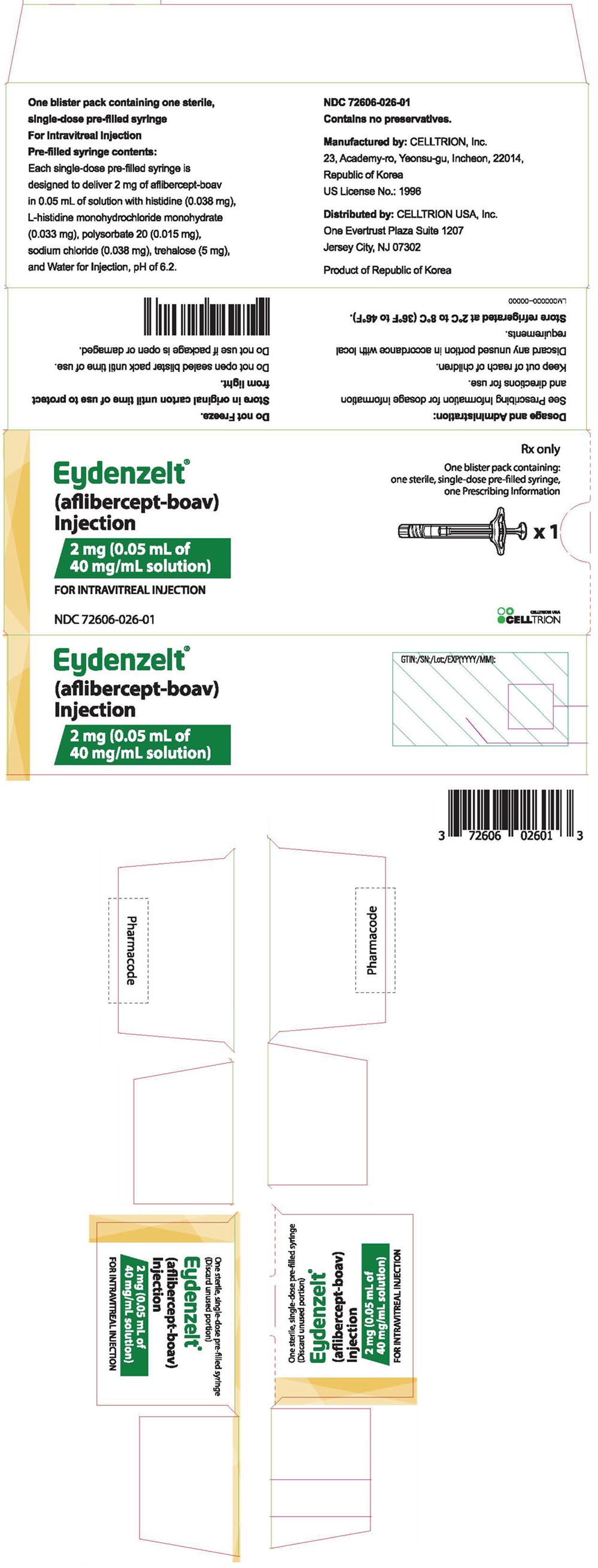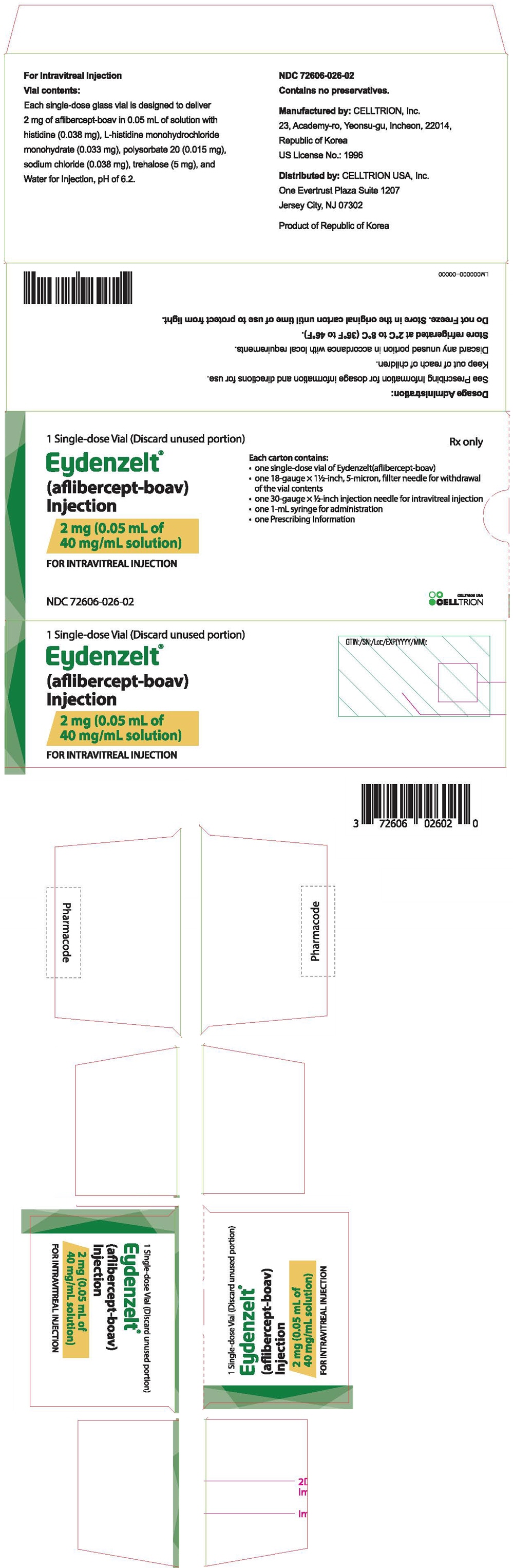 DRUG LABEL: EYDENZELT
NDC: 72606-026 | Form: INJECTION
Manufacturer: CELLTRION USA, Inc.
Category: prescription | Type: HUMAN PRESCRIPTION DRUG LABEL
Date: 20251017

ACTIVE INGREDIENTS: aflibercept 2 mg/0.05 mL
INACTIVE INGREDIENTS: HISTIDINE; HISTIDINE MONOHYDROCHLORIDE MONOHYDRATE; sodium chloride; trehalose; polysorbate 20; water

HIGHLIGHTS OF PRESCRIBING INFORMATION

These highlights do not include all the information needed to use EYDENZELT safely and effectively. See full prescribing information for EYDENZELT.
EYDENZELT® (aflibercept-boav) injection, for intravitreal use
Initial U.S. Approval: 2025
EYDENZELT® (aflibercept-boav) is biosimilar [Biosimilar means that the biological product is approved based on data demonstrating that it is highly similar to an FDA-approved biological product, known as a reference product, and that there are no clinically meaningful differences between the biosimilar product and the reference product. Biosimilarity of EYDENZELT has been demonstrated for the condition(s) of use (e.g., indication(s), dosing regimen(s)), strength(s), dosage form(s), and route(s) of administration described in its Full Prescribing Information.] to EYLEA® (aflibercept)

1 INDICATIONS AND USAGE

EYDENZELT is a vascular endothelial growth factor (VEGF) inhibitor indicated for the treatment of patients with:

- Neovascular (Wet) Age-Related Macular Degeneration (AMD) (1.1)
- Macular Edema Following Retinal Vein Occlusion (RVO) (1.2)
- Diabetic Macular Edema (DME) (1.3)
- Diabetic Retinopathy (DR) (1.4)

2 DOSAGE AND ADMINISTRATION

- Neovascular (Wet) Age-Related Macular Degeneration (AMD)
  - The recommended dose for EYDENZELT is 2 mg (0.05 mL of 40 mg/mL solution) administered by intravitreal injection every 4 weeks (approximately every 28 days, monthly) for the first 3 months, followed by 2 mg (0.05 mL of 40 mg/mL solution) via intravitreal injection once every 8 weeks (2 months). (2.5)
  - Although EYDENZELT may be dosed as frequently as 2 mg every 4 weeks (approximately every 25 days, monthly), additional efficacy was not demonstrated in most patients when aflibercept was dosed every 4 weeks compared to every 8 weeks. Some patients may need every 4 week (monthly) dosing after the first 12 weeks (3 months). (2.5)
  - Although not as effective as the recommended every 8 week dosing regimen, patients may also be treated with one dose every 12 weeks after one year of effective therapy. Patients should be assessed regularly. (2.5)
- Macular Edema Following Retinal Vein Occlusion (RVO)
  - The recommended dose for EYDENZELT is 2 mg (0.05 mL of 40 mg/mL solution) administered by intravitreal injection once every 4 weeks (approximately every 25 days, monthly). (2.6)
- Diabetic Macular Edema (DME) and Diabetic Retinopathy (DR)
  - The recommended dose for EYDENZELT is 2 mg (0.05 mL of 40 mg/mL solution) administered by intravitreal injection every 4 weeks (approximately every 28 days, monthly) for the first 5 injections followed by 2 mg (0.05 mL of 40 mg/mL solution) via intravitreal injection once every 8 weeks (2 months). (2.7, 2.8)
  - Although EYDENZELT may be dosed as frequently as 2 mg every 4 weeks (approximately every 25 days, monthly), additional efficacy was not demonstrated in most patients when aflibercept was dosed every 4 weeks compared to every 8 weeks. Some patients may need every 4 week (monthly) dosing after the first 20 weeks (5 months). (2.7, 2.8)

3 DOSAGE FORMS AND STRENGTHS

- Injection: 2 mg (0.05 mL of 40 mg/mL) solution in a single-dose pre-filled syringe (3)
- Injection: 2 mg (0.05 mL of 40 mg/mL) solution in a single-dose vial (3).

4 CONTRAINDICATIONS

- Ocular or periocular infection (4.1)
- Active intraocular inflammation (4.2)
- Hypersensitivity (4.3)

5 WARNINGS AND PRECAUTIONS

- Endophthalmitis, retinal detachments, and retinal vasculitis with or without occlusion may occur following intravitreal injections. Patients and/or caregivers should be instructed to report any signs and/or symptoms suggestive of endophthalmitis, retinal detachment, or retinal vasculitis without delay and should be managed appropriately. (5.1)
- Increases in intraocular pressure have been seen within 60 minutes of an intravitreal injection. (5.2)
- There is a potential risk of arterial thromboembolic events following intravitreal use of VEGF inhibitors. (5.3)

6 ADVERSE REACTIONS

The most common adverse reactions (≥5%) reported in patients receiving aflibercept were conjunctival hemorrhage, eye pain, cataract, vitreous detachment, vitreous floaters, and intraocular pressure increased. (6.1)

To report SUSPECTED ADVERSE REACTIONS, contact CELLTRION USA INC. at 1-800-560-9414 or FDA at 1-800-FDA-1088 or www.fda.gov/medwatch.

FULL PRESCRIBING INFORMATION

1 INDICATIONS AND USAGE

EYDENZELT is indicated for the treatment of:

2 DOSAGE AND ADMINISTRATION

2.1 Important Injection Instructions

For ophthalmic intravitreal injection. EYDENZELT must only be administered by a qualified physician.

Pre-filled Syringe: A 30-gauge × ½-inch sterile injection needle is needed but not provided.

Vial: A 5-micron sterile filter needle (18-gauge × 1½-inch), a 1-mL Luer lock syringe and a 30-gauge × ½-inch sterile injection needle are needed.

EYDENZELT is available packaged as follows:

- Pre-filled Syringe
- Vial Kit with Injection Components (filter needle, syringe, injection needle)

[see How Supplied/Storage and Handling (16)].

2.2 Neovascular (Wet) Age-Related Macular Degeneration (AMD)

The recommended dose for EYDENZELT is 2 mg (0.05 mL of 40 mg/mL solution) administered by intravitreal injection every 4 weeks (approximately every 28 days, monthly) for the first 12 weeks (3 months), followed by 2 mg (0.05 mL of 40 mg/mL solution) via intravitreal injection once every 8 weeks (2 months). Although EYDENZELT may be dosed as frequently as 2 mg every 4 weeks (approximately every 25 days, monthly), additional efficacy was not demonstrated in most patients when aflibercept was dosed every 4 weeks compared to every 8 weeks [see Clinical Studies (14.1)]. Some patients may need every 4 week (monthly) dosing after the first 12 weeks (3 months). Although not as effective as the recommended every 8 week dosing regimen, patients may also be treated with one dose every 12 weeks after one year of effective therapy. Patients should be assessed regularly.

2.3 Macular Edema Following Retinal Vein Occlusion (RVO)

The recommended dose for EYDENZELT is 2 mg (0.05 mL of 40 mg/mL solution) administered by intravitreal injection once every 4 weeks (approximately every 25 days, monthly) [see Clinical Studies (14.2), (14.3)].

2.4 Diabetic Macular Edema (DME)

The recommended dose for EYDENZELT is 2 mg (0.05 mL of 40 mg/mL solution) administered by intravitreal injection every 4 weeks (approximately every 28 days, monthly) for the first 5 injections, followed by 2 mg (0.05 mL of 40 mg/mL solution) via intravitreal injection once every 8 weeks (2 months). Although EYDENZELT may be dosed as frequently as 2 mg every 4 weeks (approximately every 25 days, monthly), additional efficacy was not demonstrated in most patients when aflibercept was dosed every 4 weeks compared to every 8 weeks [see Clinical Studies (14.4)]. Some patients may need every 4 week (monthly) dosing after the first 20 weeks (5 months).

2.5 Diabetic Retinopathy (DR)

The recommended dose for EYDENZELT is 2 mg (0.05 mL of 40 mg/mL solution) administered by intravitreal injection every 4 weeks (approximately every 28 days, monthly) for the first 5 injections, followed by 2 mg (0.05 mL of 40 mg/mL solution) via intravitreal injection once every 8 weeks (2 months). Although EYDENZELT may be dosed as frequently as 2 mg every 4 weeks (approximately every 25 days, monthly), additional efficacy was not demonstrated in most patients when aflibercept was dosed every 4 weeks compared to every 8 weeks [see Clinical Studies (14.5)]. Some patients may need every 4 week (monthly) dosing after the first 20 weeks (5 months).

2.6 Preparation for Administration - Pre-filled Syringe

The EYDENZELT pre-filled syringe is sterile and for one-time use in one eye only. It should be inspected visually prior to administration. Do not use if particulates, cloudiness, or discoloration are visible, or if the package is open or damaged. Do not use if any part of the pre-filled syringe is damaged or if the syringe cap is detached from the Luer lock.

The intravitreal injection should be performed with a 30-gauge × ½-inch injection needle (not included).

The pre-filled syringe contains more than the recommended dose of 2 mg aflibercept-boav (equivalent to 0.05 mL). Discard the excess volume prior to administration.

PRE-FILLED SYRINGE DESCRIPTION – Figure 1:

Use aseptic technique to carry out the following steps.

1. Open the Carton.

When ready to administer EYDENZELT, open the carton and remove sterilized blister pack. Carefully peel open the sterilized blister pack ensuring the sterility of its contents. Keep the pre-filled syringe in the sterilized blister pack until you are ready for assembly.

2. Remove the Pre-filled Syringe.

Using aseptic technique, remove the pre-filled syringe from the sterilized blister pack.

3. Twist Off the Syringe Cap.

Twist off (do not snap off) the syringe cap by holding the pre-filled syringe in one hand and the syringe cap with the thumb and forefinger of the other hand (see Figure 2).
Note: To avoid compromising the sterility of the product, do not pull back on the plunger.

Figure 2:

4. Attach the Needle to the Pre-filled Syringe.

Using aseptic technique, firmly twist a 30-gauge × ½-inch injection needle onto the Luer lock syringe tip (see Figure 3).

Figure 3:

Note: When ready to administer EYDENZELT, remove the plastic needle shield from the needle.

5. Check for Air Bubbles.

Hold the pre-filled syringe with the needle pointing up and check the pre-filled syringe for bubbles (see Figure 4a). If there are bubbles, gently tap the pre-filled syringe with your finger until the bubbles rise to the top (see Figure 4b).

Figure 4a:

Figure 4b:

6. Remove Air bubbles and Set the Dose.

To remove all bubbles and to expel excess drug, SLOWLY depress the plunger rod to align the plunger dome edge (see Figure 5a) with the dosing marker shown on the barrel of the pre-filled syringe (equivalent to 0.05 mL) (see Figure 5b).

Figure 5a:

Figure 5b:

7. The pre-filled syringe is for one-time use is one eye only. After injection any unused product must be discarded.

2.7 Preparation for Administration - Vial

EYDENZELDT should be inspected visually prior to administration. If particulates, cloudiness, or discoloration are visible, the vial must not be used.

The glass vial is for one-time use in one eye only.

Use aseptic technique to carry out the following preparation steps:

Prepare for intravitreal injection with the following medical devices for single use (included):

- a 5 micron sterile filter needle (18-gauge × 1 ½ inch)
- a 1 mL sterile Luer lock Syringe (with marking to measure 0.05 mL)
- a sterile injection needle (30-gauge × ½ inch)

1. Remove the protective plastic cap from the vial (see Figure 6).

Figure 6:

2. Disinfect the top of the vial with an alcohol wipe (see Figure 7).

Figure 7:

3. Remove the 18-gauge × 1½-inch, 5-micron, filter needle and the 1-mL syringe from their packaging. Attach the filter needle to the syringe by twisting it onto the Luer lock syringe tip (see Figure 8).

Figure 8:

4. Push the filter needle into the center of the vial stopper until the needle is completely inserted into the vial and the tip touches the bottom or bottom edge of the vial.

5. Using aseptic technique withdraw all of the EYDENZELDT vial contents into the syringe, keeping the vial in an upright position, slightly inclined to ease complete withdrawal. To deter the introduction of air, ensure the bevel of the filter needle is submerged into the liquid. Continue to tilt the vial during withdrawal keeping the bevel of the filter needle submerged in the liquid (see Figure 9).

Figure 9:

6. Ensure that the plunger rod is drawn sufficiently back when emptying the vial in order to completely empty the filter needle.

7. Remove the filter needle from the syringe and properly dispose of the filter needle.
Note: Filter needle is not to be used for intravitreal injection.

8. Remove the 30-gauge × ½-inch injection needle from its packaging and attach the injection needle to the syringe by firmly twisting the injection needle onto the Luer lock syringe tip (see Figure 10).

Figure 10:

9. When ready to administer EYDENZELT, remove the plastic needle cap from the needle (see Figure 11).

Figure 11:

10. Holding the syringe with the needle pointing up, check the syringe for bubbles. If there are bubbles, gently tap the syringe with your finger until the bubbles rise to the top (see Figure 12).

Figure 12:

11. To remove all of the air bubbles and to expel excess drug, SLOWLY depress the plunger so that the plunger tip aligns with the line that marks 0.05 mL on the syringe (see Figure 13).

Figure 13:

2.8 Injection Procedure

The intravitreal injection procedure should be carried out under controlled aseptic conditions, which include surgical hand disinfection and the use of sterile gloves, a sterile drape, and a sterile eyelid speculum (or equivalent). Adequate anesthesia and a topical broad–spectrum microbicide should be given prior to the injection.

Pre-filled syringe: Inject by pressing the plunger carefully and with constant pressure. Do not apply additional pressure once the plunger has reached the bottom of the syringe. A small residual volume may remain in the syringe after a full dose has been injected. This is normal. Do not administer any residual solution observed in the syringe.

Immediately following the intravitreal injection, patients should be monitored for elevation in intraocular pressure. Appropriate monitoring may consist of a check for perfusion of the optic nerve head or tonometry. If required, a sterile paracentesis needle should be available.

Following intravitreal injection, patients and/or caregivers should be instructed to report any signs and/or symptoms suggestive of endophthalmitis or retinal detachment (e.g., eye pain, redness of the eye, photophobia, blurring of vision) without delay [see Patient Counseling Information (17)].

Each sterile, pre-filled syringe or vial should only be used for the treatment of a single eye. If the contralateral eye requires treatment, a new sterile, pre-filled syringe or vial should be used and the sterile field, syringe, gloves, drapes, eyelid speculum, filter, and injection needles should be changed before EYDENZELT is administered to the other eye.

After injection, any unused product must be discarded.

3 DOSAGE FORMS AND STRENGTHS

EYDENZELT is a clear to slightly opalescent, colorless to very pale brownish-yellow solution available as

- Injection: 2 mg (0.05 mL of a 40 mg/mL solution) in a single-dose pre-filled syringe
- Injection: 2 mg (0.05 mL of a 40 mg/mL solution) in a single-dose glass vial

4 CONTRAINDICATIONS

4.1 Ocular or Periocular Infections

EYDENZELT is contraindicated in patients with ocular or periocular infections.

4.2 Active Intraocular Inflammation

EYDENZELT is contraindicated in patients with active intraocular inflammation.

4.3 Hypersensitivity

EYDENZELT is contraindicated in patients with known hypersensitivity to aflibercept or any of the excipients in EYDENZELT. Hypersensitivity reactions may manifest as rash, pruritus, urticaria, severe anaphylactic/anaphylactoid reactions, or severe intraocular inflammation.

5 WARNINGS AND PRECAUTIONS

5.1 Endophthalmitis, Retinal Detachments, and Retinal Vasculitis with or without Occlusion

Intravitreal injections, including those with aflibercept products, have been associated with endophthalmitis and retinal detachments [see Adverse Reactions (6.1)] and, more rarely, retinal vasculitis with or without occlusion [see Adverse Reactions (6.2)]. Proper aseptic injection technique must always be used when administering EYDENZELT. Patients and/or caregivers should be instructed to report any signs and/or symptoms suggestive of endophthalmitis, retinal detachment, or retinal vasculitis without delay and should be managed appropriately [see Dosage and Administration (2.4) and Patient Counseling Information (17)].

5.2 Increase in Intraocular Pressure

Acute increases in intraocular pressure have been seen within 60 minutes of intravitreal injection, including with aflibercept products [see Adverse Reactions (6.1)]. Sustained increases in intraocular pressure have also been reported after repeated intravitreal dosing with vascular endothelial growth factor (VEGF) inhibitors. Intraocular pressure and the perfusion of the optic nerve head should be monitored and managed appropriately [see Dosage and Administration (2.4)].

5.3 Thromboembolic Events

There is a potential risk of arterial thromboembolic events (ATEs) following intravitreal use of VEGF inhibitors, including aflibercept products. ATEs are defined as nonfatal stroke, nonfatal myocardial infarction, or vascular death (including deaths of unknown cause). The incidence of reported thromboembolic events in wet AMD studies during the first year was 1.8% (32 out of 1824) in the combined group of patients treated with aflibercept compared with 1.5% (9 out of 595) in patients treated with ranibizumab; through 96 weeks, the incidence was 3.3% (60 out of 1824) in the aflibercept group compared with 3.2% (19 out of 595) in the ranibizumab group. The incidence in the DME studies from baseline to week 52 was 3.3% (19 out of 578) in the combined group of patients treated with aflibercept compared with 2.8% (8 out of 287) in the control group; from baseline to week 100, the incidence was 6.4% (37 out of 578) in the combined group of patients treated with aflibercept compared with 4.2% (12 out of 287) in the control group. There were no reported thromboembolic events in the patients treated with aflibercept in the first six months of the RVO studies.

6 ADVERSE REACTIONS

The following potentially serious adverse reactions are described elsewhere in the labeling:

- Hypersensitivity [see Contraindications (4.3)]
- Endophthalmitis, Retinal Detachments, and Retinal Vasculitis with or without Occlusion [see Warnings and Precautions (5.1)]
- Increase in intraocular pressure [see Warnings and Precautions (5.2)]
- Thromboembolic events [see Warnings and Precautions (5.3)]

6.1 Clinical Trials Experience

Because clinical trials are conducted under widely varying conditions, adverse reaction rates observed in the clinical trials of a drug cannot be directly compared to rates in other clinical trials of the same or another drug and may not reflect the rates observed in practice.

A total of 2980 adult patients treated with aflibercept constituted the safety population in eight phase 3 studies. Among those, 2379 patients were treated with the recommended dose of 2 mg. Serious adverse reactions related to the injection procedure have occurred in <0.1% of intravitreal injections with aflibercept including endophthalmitis and retinal detachment. The most common adverse reactions (≥5%) reported in patients receiving aflibercept were conjunctival hemorrhage, eye pain, cataract, vitreous detachment, vitreous floaters, and intraocular pressure increased.

Neovascular (Wet) Age-Related Macular Degeneration (AMD)

The data described below reflect exposure to aflibercept in 1824 patients with wet AMD, including 1223 patients treated with the 2-mg dose, in 2 double-masked, controlled clinical studies (VIEW1 and VIEW2) for 24 months (with active control in year 1) [see Clinical Studies (14.1)].

Safety data observed in the aflibercept group in a 52-week, double-masked, Phase 2 study were consistent with these results.

Table 1: Most Common Adverse Reactions (≥1%) in Wet AMD Studies
Adverse Reactions | Baseline to Week 52 |  | Baseline to Week 96
Adverse Reactions | Aflibercept (N=1824) | Active Control (ranibizumab) (N=595) | Aflibercept (N=1824) | Control (ranibizumab) (N=595)
Conjunctival hemorrhage | 25% | 28% | 27% | 30%
Eye pain | 9% | 9% | 10% | 10%
Cataract | 7% | 7% | 13% | 10%
Vitreous detachment | 6% | 6% | 8% | 8%
Vitreous floaters | 6% | 7% | 8% | 10%
Intraocular pressure increased | 5% | 7% | 7% | 11%
Ocular hyperemia | 4% | 8% | 5% | 10%
Corneal epithelium defect | 4% | 5% | 5% | 6%
Detachment of the retinal pigment epithelium | 3% | 3% | 5% | 5%
Injection site pain | 3% | 3% | 3% | 4%
Foreign body sensation in eyes | 3% | 4% | 4% | 4%
Lacrimation increased | 3% | 1% | 4% | 2%
Vision blurred | 2% | 2% | 4% | 3%
Intraocular inflammation | 2% | 3% | 3% | 4%
Retinal pigment epithelium tear | 2% | 1% | 2% | 2%
Injection site hemorrhage | 1% | 2% | 2% | 2%
Eyelid edema | 1% | 2% | 2% | 3%
Corneal edema | 1% | 1% | 1% | 1%
Retinal detachment | <1% | <1% | 1% | 1%

Less common serious adverse reactions reported in <1% of the patients treated with aflibercept were hypersensitivity, retinal tear, and endophthalmitis.

Macular Edema Following Retinal Vein Occlusion (RVO)

The data described below reflect 6 months exposure to aflibercept with a monthly 2 mg dose in 218 patients following central retinal vein occlusion (CRVO) in 2 clinical studies (COPERNICUS and GALILEO) and 91 patients following branch retinal vein occlusion (BRVO) in one clinical study (VIBRANT) [see Clinical Studies (14.2), (14.3)].

Table 2: Most Common Adverse Reactions (≥1%) in RVO Studies
Adverse Reactions | CRVO |  | BRVO
 | Aflibercept (N=218) | Control (N=142) | Aflibercept (N=91) | Control (N=92)
Eye pain | 13% | 5% | 4% | 5%
Conjunctival hemorrhage | 12% | 11% | 20% | 4%
Intraocular pressure increased | 8% | 6% | 2% | 0%
Corneal epithelium defect | 5% | 4% | 2% | 0%
Vitreous floaters | 5% | 1% | 1% | 0%
Ocular hyperemia | 5% | 3% | 2% | 2%
Foreign body sensation in eyes | 3% | 5% | 3% | 0%
Vitreous detachment | 3% | 4% | 2% | 0%
Lacrimation increased | 3% | 4% | 3% | 0%
Injection site pain | 3% | 1% | 1% | 0%
Vision blurred | 1% | <1% | 1% | 1%
Intraocular inflammation | 1% | 1% | 0% | 0%
Cataract | <1% | 1% | 5% | 0%
Eyelid edema | <1% | 1% | 1% | 0%

Less common adverse reactions reported in <1% of the patients treated with aflibercept in the CRVO studies were corneal edema, retinal tear, hypersensitivity, and endophthalmitis.

Diabetic Macular Edema (DME) and Diabetic Retinopathy (DR)

The data described below reflect exposure to aflibercept in 578 patients with DME treated with the 2-mg dose in 2 double-masked, controlled clinical studies (VIVID and VISTA) from baseline to week 52 and from baseline to week 100 [see Clinical Studies (14.4)].

Table 3: Most Common Adverse Reactions (≥1%) in DME Studies
Adverse Reactions | Baseline to Week 52 |  | Baseline to Week 100
Adverse Reactions | Aflibercept (N=578) | Control (N=287) | Aflibercept (N=578) | Control (N=287)
Conjunctival hemorrhage | 28% | 17% | 31% | 21%
Eye pain | 9% | 6% | 11% | 9%
Cataract | 8% | 9% | 19% | 17%
Vitreous floaters | 6% | 3% | 8% | 6%
Corneal epithelium defect | 5% | 3% | 7% | 5%
Intraocular pressure increased | 5% | 3% | 9% | 5%
Ocular hyperemia | 5% | 6% | 5% | 6%
Vitreous detachment | 3% | 3% | 8% | 6%
Foreign body sensation in eyes | 3% | 3% | 3% | 3%
Lacrimation increased | 3% | 2% | 4% | 2%
Vision blurred | 2% | 2% | 3% | 4%
Intraocular inflammation | 2% | <1% | 3% | 1%
Injection site pain | 2% | <1% | 2% | <1%
Eyelid edema | <1% | 1% | 2% | 1%

Less common adverse reactions reported in <1% of the patients treated with aflibercept were hypersensitivity, retinal detachment, retinal tear, corneal edema, and injection site hemorrhage.

Safety data observed in 269 patients with nonproliferative diabetic retinopathy (NPDR) through week 52 in the PANORAMA trial were consistent with those seen in the phase 3 VIVID and VISTA trials (see Table 3 above).

6.2 Postmarketing Experience

The following adverse reactions have been identified during postapproval use of aflibercept. Because these reactions are reported voluntarily from a population of uncertain size, it is not always possible to reliably estimate their frequency or establish a causal relationship to drug exposure.

Eye disorders: retinal vasculitis and occlusive retinal vasculitis related to intravitreal injection with aflibercept (reported at a rate of 0.6 and 0.2 per 1 million injections, respectively, based on postmarketing experience from November 2011 until November 2023).

8 USE IN SPECIFIC POPULATIONS

8.1 Pregnancy

Risk Summary

Adequate and well-controlled studies with aflibercept have not been conducted in pregnant women. Aflibercept produced adverse embryofetal effects in rabbits, including external, visceral, and skeletal malformations. A fetal No Observed Adverse Effect Level (NOAEL) was not identified. At the lowest dose shown to produce adverse embryofetal effects, systemic exposures (based on AUC for free aflibercept) were approximately 6 times higher than AUC values observed in humans after a single intravitreal treatment at the recommended clinical dose [see Animal Data].

Animal reproduction studies are not always predictive of human response, and it is not known whether aflibercept can cause fetal harm when administered to a pregnant woman. Based on the anti-VEGF mechanism of action for aflibercept [see Clinical Pharmacology (12.1)], treatment with aflibercept may pose a risk to human embryofetal development. EYDENZELT should be used during pregnancy only if the potential benefit justifies the potential risk to the fetus.

All pregnancies have a background risk of birth defect, loss, or other adverse outcomes. The background risk of major birth defects and miscarriage for the indicated population is unknown. In the U.S. general population, the estimated background risk of major birth defects and miscarriage in clinically recognized pregnancies is 2-4% and 15-20%, respectively.

Data

Animal Data

In two embryofetal development studies, aflibercept produced adverse embryofetal effects when administered every three days during organogenesis to pregnant rabbits at intravenous doses ≥3 mg per kg, or every six days during organogenesis at subcutaneous doses ≥0.1 mg per kg.

Adverse embryofetal effects included increased incidences of postimplantation loss and fetal malformations, including anasarca, umbilical hernia, diaphragmatic hernia, gastroschisis, cleft palate, ectrodactyly, intestinal atresia, spina bifida, encephalomeningocele, heart and major vessel defects, and skeletal malformations (fused vertebrae, sternebrae, and ribs; supernumerary vertebral arches and ribs; and incomplete ossification). The maternal No Observed Adverse Effect Level (NOAEL) in these studies was 3 mg per kg. Aflibercept produced fetal malformations at all doses assessed in rabbits and the fetal NOAEL was not identified. At the lowest dose shown to produce adverse embryofetal effects in rabbits (0.1 mg per kg), systemic exposure (AUC) of free aflibercept was approximately 6 times higher than systemic exposure (AUC) observed in adult patients after a single intravitreal dose of 2 mg.

8.2 Lactation

Risk Summary

There is no information regarding the presence of aflibercept products in human milk, the effects of the drug on the breastfed infant, or the effects of the drug on milk production/excretion. Because many drugs are excreted in human milk, and because the potential for absorption and harm to infant growth and development exists, EYDENZELT is not recommended during breastfeeding.

The developmental and health benefits of breastfeeding should be considered along with the mother's clinical need for EYDENZELT and any potential adverse effects on the breastfed child from EYDENZELT.

8.3 Females and Males of Reproductive Potential

Contraception

Females of reproductive potential are advised to use effective contraception prior to the initial dose, during treatment, and for at least 3 months after the last intravitreal injection of EYDENZELT.

Infertility

There are no data regarding the effects of aflibercept on human fertility. Aflibercept adversely affected female and male reproductive systems in cynomolgus monkeys when administered by intravenous injection at a dose approximately 1500 times higher than the systemic level observed in adult patients with an intravitreal dose of 2 mg. A No Observed Adverse Effect Level (NOAEL) was not identified. These findings were reversible within 20 weeks after cessation of treatment [see Nonclinical Toxicology (13.1)].

8.4 Pediatric Use

A pediatric assessment for EYDENZELT demonstrates that EYDENZELT is safe and effective for pediatric patients in an indication for which EYLEA (aflibercept) is approved. However, EYDENZELT is not approved for such indication due to marketing exclusivity for EYLEA (aflibercept).

8.5 Geriatric Use

In the clinical studies, approximately 76% (2049/2701) of patients randomized to treatment with aflibercept were ≥65 years of age and approximately 46% (1250/2701) were ≥75 years of age. No significant differences in efficacy or safety were seen with increasing age in these studies.

10 OVERDOSAGE

Overdosing with increased injection volume may increase intraocular pressure. Therefore, in case of overdosage, intraocular pressure should be monitored and if deemed necessary by the treating physician, adequate treatment should be initiated.

11 DESCRIPTION

Aflibercept-boav is a recombinant fusion protein consisting of portions of human VEGF receptors 1 and 2 extracellular domains fused to the Fc portion of human IgG1 formulated as an iso-osmotic solution for intravitreal administration. Aflibercept-boav is a dimeric glycoprotein with a protein molecular weight of 97 kilodaltons (kDa) and contains glycosylation, constituting an additional 15% of the total molecular mass, resulting in a total molecular weight of 115 kDa. Aflibercept-boav is produced in recombinant Chinese hamster ovary (CHO) cells.

EYDENZELT (aflibercept-boav) injection is a sterile, clear to slightly opalescent, and colorless to very pale brownish-yellow solution. EYDENZELT does not contain anti-microbial preservative and is supplied as a sterile, aqueous solution for intravitreal injection in a single-dose, pre-filled syringe or a single-dose glass vial designed to deliver 0.05 mL of solution containing 2 mg of aflibercept-boav in histidine (0.038 mg), L-histidine monohydrochloride monohydrate (0.033 mg), polysorbate 20 (0.015 mg), sodium chloride (0.038 mg), trehalose (5 mg) and water for injection with a pH of 6.2.

12 CLINICAL PHARMACOLOGY

12.1 Mechanism of Action

Vascular endothelial growth factor-A (VEGF-A) and placental growth factor (PlGF) are members of the VEGF family of angiogenic factors that can act as mitogenic, chemotactic, and vascular permeability factors for endothelial cells. VEGF acts via two receptor tyrosine kinases, VEGFR-1 and VEGFR-2, present on the surface of endothelial cells. PlGF binds only to VEGFR-1, which is also present on the surface of leucocytes. Activation of these receptors by VEGF-A can result in neovascularization and vascular permeability.

Aflibercept products act as a soluble decoy receptor that binds VEGF-A and PlGF, and thereby can inhibit the binding and activation of these cognate VEGF receptors.

12.2 Pharmacodynamics

Neovascular (Wet) Age-Related Macular Degeneration (AMD)

In the clinical studies anatomic measures of disease activity improved similarly in all treatment groups from baseline to week 52. Anatomic data were not used to influence treatment decisions during the first year.

Macular Edema Following Retinal Vein Occlusion (RVO)

Reductions in mean retinal thickness were observed in COPERNICUS, GALILEO, and VIBRANT at week 24 compared to baseline. Anatomic data were not used to influence treatment decisions [see Clinical Studies (14.2), (14.3)].

Diabetic Macular Edema (DME)

Reductions in mean retinal thickness were observed in VIVID and VISTA at weeks 52 and 100 compared to baseline. Anatomic data were not used to influence aflibercept treatment decisions [see Clinical Studies (14.4)].

12.3 Pharmacokinetics

Aflibercept is administered intravitreally to exert local effects in the eye. In patients with wet AMD, RVO, or DME, following intravitreal administration of aflibercept, a fraction of the administered dose is expected to bind with endogenous VEGF in the eye to form an inactive aflibercept: VEGF complex. Once absorbed into the systemic circulation, aflibercept presents in the plasma as free aflibercept (unbound to VEGF) and a more predominant stable inactive form with circulating endogenous VEGF (i.e., aflibercept: VEGF complex).

Absorption/Distribution

Following intravitreal administration of 2 mg per eye of aflibercept to patients with wet AMD, RVO, and DME, the mean Cmax of free aflibercept in the plasma was 0.02 mcg/mL (range: 0 to 0.054 mcg/mL), 0.05 mcg/mL (range: 0 to 0.081 mcg/mL), and 0.03 mcg/mL (range: 0 to 0.076 mcg/mL), respectively and was attained in 1 to 3 days. The free aflibercept plasma concentrations were undetectable two weeks post-dosing in all patients. Aflibercept did not accumulate in plasma when administered as repeated doses intravitreally every 4 weeks. It is estimated that after intravitreal administration of 2 mg to patients, the mean maximum plasma concentration of free aflibercept is more than 100 fold lower than the concentration of aflibercept required to half-maximally bind systemic VEGF.

The volume of distribution of free aflibercept following intravenous (I.V.) administration of aflibercept has been determined to be approximately 6L.

Metabolism/Elimination

Aflibercept is a therapeutic protein and no drug metabolism studies have been conducted. Aflibercept is expected to undergo elimination through both target-mediated disposition via binding to free endogenous VEGF and metabolism via proteolysis. The terminal elimination half-life (t1/2) of free aflibercept in plasma was approximately 5 to 6 days after I.V. administration of doses of 2 to 4 mg/kg aflibercept.

Specific Populations

Renal Impairment

Pharmacokinetic analysis of a subgroup of patients (n=492) in one wet AMD study, of which 43% had renal impairment (mild n=120, moderate n=74, and severe n=16), revealed no differences with respect to plasma concentrations of free aflibercept after intravitreal administration every 4 or 8 weeks. Similar results were seen in patients in a RVO study and in patients in a DME study. No dose adjustment based on renal impairment status is needed for either wet AMD, RVO, or DME patients.

Other

No dosage modification is required based on gender or in the elderly.

12.6 Immunogenicity

The observed incidence of anti-drug antibodies is highly dependent on the sensitivity and specificity of the assay. Differences in assay methods preclude meaningful comparisons of the incidence of anti-drug antibodies in the studies described below with the incidence of anti-drug antibodies in other studies, including those of aflibercept or of other aflibercept products.

In the wet AMD, RVO, and DME studies, the pre-treatment incidence of immunoreactivity to aflibercept was approximately 1% to 3% across treatment groups. After dosing with aflibercept for 24-100 weeks, antibodies to aflibercept were detected in a similar percentage range of patients.

There were no differences in efficacy or safety between patients with or without immunoreactivity.

13 NONCLINICAL TOXICOLOGY

13.1 Carcinogenesis, Mutagenesis, Impairment of Fertility

No studies have been conducted on the mutagenic or carcinogenic potential of aflibercept products. Effects on male and female fertility were assessed as part of a 6-month study in monkeys with intravenous administration of aflibercept at weekly doses ranging from 3 to 30 mg per kg.

Absent or irregular menses associated with alterations in female reproductive hormone levels and changes in sperm morphology and motility were observed at all dose levels. In addition, females showed decreased ovarian and uterine weight accompanied by compromised luteal development and reduction of maturing follicles. These changes correlated with uterine and vaginal atrophy. A No Observed Adverse Effect Level (NOAEL) was not identified. Intravenous administration of the lowest dose of aflibercept assessed in monkeys (3 mg per kg) resulted in systemic exposure (AUC) for free aflibercept that was approximately 1500 times higher than the systemic exposure observed in adult patients after an intravitreal dose of 2 mg. All changes were reversible within 20 weeks after cessation of treatment.

13.2 Animal Toxicology and/or Pharmacology

Erosions and ulcerations of the respiratory epithelium in nasal turbinates in monkeys treated with aflibercept intravitreally were observed at intravitreal doses of 2 or 4 mg per eye. At the NOAEL of 0.5 mg per eye in monkeys, the systemic exposure (AUC) was 56 times higher than the exposure observed in adult patients after an intravitreal dose of 2 mg. Similar effects were not seen in clinical studies [see Clinical Studies (14)].

14 CLINICAL STUDIES

14.1 Neovascular (Wet) Age-Related Macular Degeneration (AMD)

The safety and efficacy of aflibercept were assessed in two randomized, multi-center, double-masked, active-controlled studies in patients with wet AMD. A total of 2412 patients were treated and evaluable for efficacy (1817 with aflibercept) in the two studies (VIEW1 and VIEW2). In each study, up to week 52, patients were randomly assigned in a 1:1:1:1 ratio to 1 of 4 dosing regimens: 1) aflibercept administered 2 mg every 8 weeks following 3 initial monthly doses (aflibercept 2Q8); 2) aflibercept administered 2 mg every 4 weeks (aflibercept 2Q4); 3) aflibercept 0.5 mg administered every 4 weeks (aflibercept 0.5Q4); and 4) ranibizumab administered 0.5 mg every 4 weeks (ranibizumab 0.5 mg Q4). Protocol-specified visits occurred every 28±3 days. Patient ages ranged from 49 to 99 years with a mean of 76 years.

In both studies, the primary efficacy endpoint was the proportion of patients who maintained vision, defined as losing fewer than 15 letters of visual acuity at week 52 compared to baseline. Both aflibercept 2Q8 and aflibercept 2Q4 groups were shown to have efficacy that was clinically equivalent to the ranibizumab 0.5 mg Q4 group in year 1.

Detailed results from the analysis of the VIEW1 and VIEW2 studies are shown in Table 4 and Figure 14 below.

Table 4: Efficacy Outcomes at Week 52 (Full Analysis Set with LOCF) in VIEW1 and VIEW2 Studies
 | VIEW1 |  |  | VIEW2
 | Aflibercept 2 mg Q8 weeks [After treatment initiation with 3 monthly doses] | Aflibercept 2 mg Q4 weeks | ranibizumab 0.5 mg Q4 weeks | Aflibercept 2 mg Q8 weeks | Aflibercept 2 mg Q4 weeks | ranibizumab 0.5 mg Q4 weeks
Full Analysis Set | N=301 | N=304 | N=304 | N=306 | N=309 | N=291
Efficacy Outcomes
Proportion of patients who maintained visual acuity (%) | 94% | 95% | 94% | 95% | 95% | 95%
(<15 letters of BCVA loss)
Difference [Aflibercept group minus the ranibizumab group] (%) | 0.6 | 1.3 |  | 0.6 | -0.3
(95.1% CI) | (-3.2, 4.4) | (-2.4, 5.0) |  | (-2.9, 4.0) | (-4.0, 3.3)
Mean change in BCVA as measured by ETDRS letter score from Baseline | 7.9 | 10.9 | 8.1 | 8.9 | 7.6 | 9.4
Difference in LS mean | 0.3 | 3.2 |  | -0.9 | -2.0
(95.1% CI) | (-2.0, 2.5) | (0.9, 5.4) |  | (-3.1, 1.3) | (-4.1, 0.2)
Number of patients who gained at least 15 letters of vision from Baseline (%) | 92 (31%) | 114 (38%) | 94 (31%) | 96 (31%) | 91 (29%) | 99 (34%)
Difference (%) | -0.4 | 6.6 |  | -2.6 | -4.6
(95.1% CI) | (-7.7, 7.0) | (-1.0, 14.1) |  | (-10.2, 4.9) | (-12.1, 2.9)
BCVA = Best Corrected Visual Acuity; CI = Confidence Interval; ETDRS = Early Treatment Diabetic Retinopathy Study; LOCF = Last Observation Carried Forward (baseline values are not carried forward); 95.1% confidence intervals were presented to adjust for safety assessment conducted during the study

Treatment effects in evaluable subgroups (e.g., age, gender, race, baseline visual acuity) in each study were in general consistent with the results in the overall populations.

Figure 14: Mean Change in Visual Acuity from Baseline to Week 96 [Patient dosing schedules were individualized from weeks 52 to 96 using a modified 12-week dosing regimen.] in VIEW1 and VIEW2 Studies

VIEW1 and VIEW2 studies were both 96 weeks in duration. However, after 52 weeks patients no longer followed a fixed dosing schedule. Between week 52 and week 96, patients continued to receive the drug and dosage strength to which they were initially randomized on a modified 12 week dosing schedule (doses at least every 12 weeks and additional doses as needed). Therefore, during the second year of these studies there was no active control comparison arm.

14.2 Macular Edema Following Central Retinal Vein Occlusion (CRVO)

The safety and efficacy of aflibercept were assessed in two randomized, multi-center, double-masked, sham-controlled studies in patients with macular edema following CRVO. A total of 358 patients were treated and evaluable for efficacy (217 with aflibercept) in the two studies (COPERNICUS and GALILEO). In both studies, patients were randomly assigned in a 3:2 ratio to either 2 mg aflibercept administered every 4 weeks (2Q4), or sham injections (control group) administered every 4 weeks for a total of 6 injections. Protocol-specified visits occurred every 28±7 days. Patient ages ranged from 22 to 89 years with a mean of 64 years.

In both studies, the primary efficacy endpoint was the proportion of patients who gained at least 15 letters in BCVA compared to baseline. At week 24, the aflibercept 2 mg Q4 group was superior to the control group for the primary endpoint.

Results from the analysis of the COPERNICUS and GALILEO studies are shown in Table 5 and Figure 15 below.

Table 5: Efficacy Outcomes at Week 24 (Full Analysis Set with LOCF) in COPERNICUS and GALILEO Studies
 | COPERNICUS |  | GALILEO
 | Control | Aflibercept 2 mg Q4 weeks | Control | Aflibercept 2 mg Q4 weeks
 | N=73 | N=114 | N=68 | N=103
Efficacy Outcomes
Proportion of patients who gained at least 15 letters in BCVA from Baseline (%) | 12% | 56% | 22% | 60%
Weighted Difference [Difference is aflibercept 2 mg Q4 weeks minus Control] , [Difference and CI are calculated using Cochran-Mantel-Haenszel (CMH) test adjusted for baseline factors; 95.1% confidence intervals were presented to adjust for the multiple assessments conducted during the study] (%) |  | 44.8% [p<0.01 compared with Control] |  | 38.3%
(95.1% CI) |  | (32.9, 56.6) |  | (24.4, 52.1)
Mean change in BCVA as measured by ETDRS letter score from Baseline (SD) | -4.0 (18.0) | 17.3 (12.8) | 3.3 (14.1) | 18.0 (12.2)
Difference in LS mean , [LS mean and CI based on an ANCOVA model] |  | 21.7 |  | 14.7
(95.1% CI) |  | (17.3, 26.1) |  | (10.7, 18.7)

Figure 15: Mean Change in BCVA as Measured by ETDRS Letter Score from Baseline to Week 24 in COPERNICUS and GALILEO Studies

Treatment effects in evaluable subgroups (e.g., age, gender, race, baseline visual acuity, retinal perfusion status, and CRVO duration) in each study and in the combined analysis were in general consistent with the results in the overall populations.

14.3 Macular Edema Following Branch Retinal Vein Occlusion (BRVO)

The safety and efficacy of aflibercept were assessed in a 24-week, randomized, multi-center, double-masked, controlled study in patients with macular edema following BRVO. A total of 181 patients were treated and evaluable for efficacy (91 with aflibercept) in the VIBRANT study. In the study, patients were randomly assigned in a 1:1 ratio to either 2 mg aflibercept administered every 4 weeks (2Q4) or laser photocoagulation administered at baseline and subsequently as needed (control group). Protocol-specified visits occurred every 28±7 days. Patient ages ranged from 42 to 94 years with a mean of 65 years.

In the VIBRANT study, the primary efficacy endpoint was the proportion of patients who gained at least 15 letters in BCVA at week 24 compared to baseline. At week 24, the aflibercept 2 mg Q4 group was superior to the control group for the primary endpoint.

Detailed results from the analysis of the VIBRANT study are shown in Table 6 and Figure 16 below.

Table 6: Efficacy Outcomes at Week 24 (Full Analysis Set with LOCF) in VIBRANT Study
 | VIBRANT
 | Control | Aflibercept 2 mg Q4 weeks
 | N=90 | N=91
Efficacy Outcomes
Proportion of patients who gained at least 15 letters in BCVA from Baseline (%) | 26.7% | 52.7%
Weighted Difference [Difference is aflibercept 2 mg Q4 weeks minus Control] , [Difference and CI are calculated using Mantel-Haenszel weighting scheme adjusted for region (North America vs. Japan) and baseline BCVA category (> 20/200 and ≤ 20/200)] (%) |  | 26.6% [p<0.01 compared with Control]
(95% CI) |  | (13.0, 40.1)
Mean change in BCVA as measured by ETDRS letter score from Baseline (SD) | 6.9 (12.9) | 17.0 (11.9)
Difference in LS mean , [LS mean and CI based on an ANCOVA model] |  | 10.5
(95% CI) |  | (7.1, 14.0)

Figure 16: Mean Change in BCVA as Measured by ETDRS Letter Score from Baseline to Week 24 in VIBRANT Study

Treatment effects in evaluable subgroups (e.g., age, gender, and baseline retinal perfusion status) in the study were in general consistent with the results in the overall populations.

14.4 Diabetic Macular Edema (DME)

The safety and efficacy of aflibercept were assessed in two randomized, multi-center, double-masked, controlled studies in patients with DME. A total of 862 randomized and treated patients were evaluable for efficacy. Protocol-specified visits occurred every 28±7 days. Patient ages ranged from 23 to 87 years with a mean of 63 years.

Of those, 576 were randomized to aflibercept groups in the two studies (VIVID and VISTA). In each study, patients were randomly assigned in a 1:1:1 ratio to 1 of 3 dosing regimens: 1) aflibercept administered 2 mg every 8 weeks following 5 initial monthly injections (aflibercept 2Q8); 2) aflibercept administered 2 mg every 4 weeks (aflibercept 2Q4); and 3) macular laser photocoagulation (at baseline and then as needed). Beginning at week 24, patients meeting a pre-specified threshold of vision loss were eligible to receive additional treatment: patients in the aflibercept groups could receive laser and patients in the laser group could receive aflibercept.

In both studies, the primary efficacy endpoint was the mean change from baseline in BCVA at week 52 as measured by ETDRS letter score. Efficacy of both aflibercept 2Q8 and aflibercept 2Q4 groups was statistically superior to the control group. This statistically superior improvement in BCVA was maintained at week 100 in both studies.

Results from the analysis of the VIVID and VISTA studies are shown in Table 7 and Figure 17 below.

Table 7: Efficacy Outcomes at Weeks 52 and 100 (Full Analysis Set with LOCF) in VIVID and VISTA Studies
 | VIVID |  |  | VISTA
 | Aflibercept 2 mg Q8 weeks [After treatment initiation with 5 monthly injections] | Aflibercept 2mg Q4 weeks | Control | Aflibercept 2 mg Q8 weeks | Aflibercept 2mg Q4 weeks | Control
Full Analysis Set | N=135 | N=136 | N=132 | N=151 | N=154 | N=154
Efficacy Outcomes at Week 52
Mean change in BCVA as measured by ETDRS letter score from Baseline (SD) | 10.7 (9.3) | 10.5 (9.6) | 1.2 (10.6) | 10.7 (8.2) | 12.5 (9.5) | 0.2 (12.5)
Difference [LS mean and CI based on an ANCOVA model with baseline BCVA measurement as a covariate and a factor for treatment group. Additionally, protocol specified stratification factors were included in the model] , [Difference is aflibercept group minus Control group] in LS mean (97.5% CI) | 9.1 [p<0.01 compared with Control] (6.3, 11.8) | 9.3 (6.5, 12.0) |  | 10.5 (7.7, 13.2) | 12.2 (9.4, 15.0)
Proportion of patients who gained at least 15 letters in BCVA from Baseline (%) | 33.3% | 32.4% | 9.1% | 31.1% | 41.6% | 7.8%
Adjusted Difference, [Difference with confidence interval (CI) and statistical test is calculated using Mantel-Haenszel weighting scheme adjusted by protocol specified stratification factors] (%) (97.5% CI) | 24.2% (13.5, 34.9) | 23.3% (12.6, 33.9) |  | 23.3% (13.5, 33.1) | 34.2% (24.1, 44.4)
Efficacy Outcomes at Week 100
Mean change in BCVA as measured by ETDRS letter score from Baseline (SD) | 9.4 (10.5) | 11.4 (11.2) | 0.7 (11.8) | 11.1 (10.7) | 11.5 (13.8) | 0.9 (13.9)
Difference, in LS mean (97.5% CI) | 8.2 (5.2, 11.3) | 10.7 (7.6, 13.8) |  | 10.1 (7.0, 13.3) | 10.6 (7.1, 14.2)
Proportion of patients who gained at least 15 letters in BCVA from Baseline (%) | 31.1% | 38.2% | 12.1% | 33.1% | 38.3% | 13.0%
Adjusted Difference, (%) (97.5% CI) | 19.0% (8.0, 29.9) | 26.1% (14.8, 37.5) |  | 20.1% (9.6, 30.6) | 25.8% (15.1, 36.6)

Figure 17: Mean Change in BCVA as Measured by ETDRS Letter Score from Baseline to Week 100 in VIVID and VISTA Studies

Treatment effects in the subgroup of patients who had previously been treated with a VEGF inhibitor prior to study participation were similar to those seen in patients who were VEGF inhibitor naïve prior to study participation.

Treatment effects in evaluable subgroups (e.g., age, gender, race, baseline HbA1c, baseline visual acuity, prior anti-VEGF therapy) in each study were in general consistent with the results in the overall populations.

14.5 Diabetic Retinopathy (DR)

Efficacy and safety data of aflibercept in diabetic retinopathy (DR) are derived from the VIVID, VISTA, and PANORAMA studies.

VIVID AND VISTA

In the VIVID and VISTA studies, an efficacy outcome was the change in the Early Treatment Diabetic Retinopathy Study (ETDRS) Diabetic Retinopathy Severity Scale (ETDRS-DRSS). The ETDRS-DRSS score was assessed at baseline and approximately every 6 months thereafter for the duration of the studies [see Clinical Studies (14.4)].

All enrolled patients had DR and DME at baseline. The majority of patients enrolled in these studies (77%) had moderate-to-severe nonproliferative diabetic retinopathy (NPDR) based on the ETDRS-DRSS. At week 100, the proportion of patients improving by at least 2 steps on the ETDRS-DRSS was significantly greater in both aflibercept treatment groups (2Q4 and 2Q8) when compared to the control group.

Results from the analysis of ETDRS-DRSS at week 100 in the VIVID and VISTA studies are shown in Table 8 below.

Table 8: Proportion of Patients Who Achieved a ≥2-Step Improvement from Baseline in the ETDRS-DRSS Score at Week 100 in VIVID and VISTA Studies
 | VIVID |  |  | VISTA
 | Aflibercept 2 mg Q8 weeks [After treatment initiation with 5 monthly injections] | Aflibercept 2mg Q4 weeks | Control | Aflibercept 2 mg Q8 weeks | Aflibercept 2mg Q4 weeks | Control
Evaluable Patients [The number of evaluable patients included all patients who had valid ETDRS-DRSS data at baseline] | N=101 | N=97 | N=99 | N=148 | N=153 | N=150
Number of patients with a ≥2-step improvement on ETDRS-DRSS from Baseline (%) | 32 | 27 | 7 | 56 | 58 | 24
Number of patients with a ≥2-step improvement on ETDRS-DRSS from Baseline (%) | (32%) | (28%) | (7%) | (38%) | (38%) | (16%)
Difference [Difference with confidence interval (CI) was calculated using Mantel-Haenszel weighting scheme adjusted by protocol specified stratification factors] , [Difference is aflibercept minus Control group] (%) | 24% [p<0.01 compared with Control] | 21% |  | 22% | 22%
(97.5% CI) | (12, 36) | (9, 33) |  | (11, 33) | (11, 33)
Non-gradable post-baseline ETDRS-DRSS values were treated as missing and were imputed using the last gradable ETDRS-DRSS values (including baseline values if all post-baseline values were missing or non-gradable)

Results of the evaluable subgroups (e.g., age, gender, race, baseline HbA1c, baseline visual acuity) on the proportion of patients who achieved a ≥2-step improvement on the ETDRS-DRSS from baseline to week 100 were, in general, consistent with those in the overall population.

PANORAMA

The PANORAMA study assessed the safety and efficacy of aflibercept in a randomized, multi-center, double-masked, controlled study in patients with moderately severe to severe nonproliferative diabetic retinopathy (NPDR) (ETDRS-DRSS of 47 or 53), without central-involved DME (CI-DME). A total of 402 randomized patients were evaluable for efficacy. Protocol-specified visits occurred every 28±7 days for the first 5 visits, then every 8 weeks (56±7 days). Patient ages ranged from 25 to 85 years with a mean of 55.7 years.

Patients were randomly assigned in a 1:1:1 ratio to 1 of 3 dosing regimens: 1) 3 initial monthly aflibercept 2 mg injections followed by one injection after 8 weeks and then one injection every 16 weeks (aflibercept 2Q16); 2) 5 monthly aflibercept 2 mg injections followed by one injection every 8 weeks (aflibercept 2Q8); and 3) sham treatment.

The primary efficacy endpoint was the proportion of patients who improved by ≥2 steps on the DRSS from baseline to week 24 in the combined aflibercept groups and at week 52 in the 2Q16 and 2Q8 groups individually versus sham. A key secondary endpoint was the proportion of patients developing the composite endpoint of proliferative diabetic retinopathy or anterior segment neovascularization through week 52.

At week 52, efficacy in the 2Q16 and 2Q8 groups was superior to the sham group (see Table 9 and Table 10). The proportion of patients with a ≥2-step improvement over time is shown in Figure 18.

Table 9: Proportion of Patients Who Achieved a ≥2-Step Improvement from Baseline in the ETDRS-DRSS Score at Weeks 24 and 52 in PANORAMA
 | PANORAMA
 | Week 24 |  | Week 52
 | Aflibercept Combined | Control (sham) | Aflibercept 2Q16 | Aflibercept 2Q8 | Control (sham)
Full Analysis Set | N=269 | N=133 | N=135 | N=134 | N=133
Proportion of patients with a ≥2-step improvement on ETDRS-DRSS from Baseline (%) | 58% | 6% | 65% | 80% | 15%
Adjusted Difference [Difference is aflibercept group minus sham] (%) (95% CI) [Difference with CI was calculated using the Mantel-Haenszel weighting scheme adjusted by baseline DRSS stratification variable] | 52% [p<0.01 compared with Control. p-value was calculated using a 2-sided Cochran-Mantel-Haenszel test adjusted by baseline DRSS stratification variable.] (45, 60) |  | 50% (40, 60) | 65% (56, 74)
Non-gradable post-baseline ETDRS-DRSS values were treated as missing and were imputed using the last gradable ETDRS-DRSS values (including baseline values if all post-baseline values were missing or non-gradable)

Figure 18: Proportion of Patients Who Achieved a ≥2-Step Improvement from Baseline in the ETDRS-DRSS Score Through Week 52 in PANORAMA

Table 10: Effect of aflibercept on Worsening of Diabetic Retinopathy in PANORAMA through Week 52
 | Aflibercept 2Q16 | Aflibercept 2Q8 | Control (Sham)
Full Analysis Set | N=135 | N=134 | N=133
Composite Endpoint of Developing PDR or ASNV [As diagnosed by either the Reading Center or Investigator through week 52]
Event Rate [Estimated using Kaplan-Meier method] | 4.0% [p<0.01 compared with Control] | 2.4% | 20.1%
Hazard Ratio | 0.15 | 0.12
Development of Proliferative Diabetic Retinopathy [Defined as ≥2-step worsening on the ETDRS-DRSS score through week 52]
Event Rate | 1.6% | 0.0% | 11.9%
Hazard Ratio | 0.11 | 0.00
PDR = Proliferative Diabetic Retinopathy; ASNV = Anterior Segment Neovascularization

16 HOW SUPPLIED/STORAGE AND HANDLING

16.1 How Supplied

Each pre-filled syringe or vial is for single eye use only. Discard unused portion. EYDENZELT injection is a clear to slightly opalescent, colorless to very pale brownish-yellow solution and is supplied in the following presentations [see Dosage and Administration (2.1), (2.2), (2.3), (2.4) and (2.8)]:

NDC NUMBER | CARTON TYPE | CARTON CONTENTS
NDC 72606-026-01 | Pre-filled Syringe | one blister pack containing one EYDENZELT 2 mg (0.05 mL of a 40 mg/mL solution) sterile, single-dose pre-filled syringe one Prescribing Information
NDC 72606-026-02 | Vial Kit with Injection Components | one EYDENZELT 2 mg (0.05 mL of a 40 mg/mL solution) single-dose glass vial one 18-gauge × 1½-inch, 5-micron, filter needle for withdrawal of the vial contents one 30-gauge × ½-inch injection needle for intravitreal injection one 1-mL syringe for administration one Prescribing Information

16.2 Storage and Handling

Refrigerate EYDENZELT at 2°C to 8ºC (36°F to 46ºF). Do not freeze. Do not use beyond the date stamped on the carton and container label. Store in the original carton until time of use to protect from light. Do not open sealed blister pack until time of use.

17 PATIENT COUNSELING INFORMATION

In the days following EYDENZELT administration, patients are at risk of developing endophthalmitis, retinal detachment, or retinal vasculitis with or without occlusion. If the eye becomes red, sensitive to light, painful, or develops a change in vision, advise patients and/or caregivers to seek immediate care from an ophthalmologist [see Warnings and Precautions (5.1)].

Patients may experience temporary visual disturbances after an intravitreal injection with EYDENZELT and the associated eye examinations [see Adverse Reactions (6)]. Advise patients not to drive or use machinery until visual function has recovered sufficiently.

Manufactured by:
CELLTRION, Inc.
23, Academy-ro, Yeonsu-gu, Incheon, 22014, Republic of Korea
U.S. License Number: 1996

Distributed by:
CELLTRION USA, Inc.
One Evertrust Plz Ste 1207, Jersey City, NJ, 07302, US

PRINCIPAL DISPLAY PANEL - 2 mg/0.05 mL Syringe Blister Pack Carton

Rx only

Eydenzelt®
(aflibercept-boav)
Injection

2 mg (0.05 mL of
40 mg/mL solution)

x 1

FOR INTRAVITREAL INJECTION

One blister pack containing:
one sterile, single-dose pre-filled syringe,
one Prescribing Information

NDC 72606-026-01

CELLTRION USA
CELLTRION

PRINCIPAL DISPLAY PANEL - 2 mg (0.05 mL of 40 mg/mL solution)

1 Single-dose Vial (Discard unused portion)

Rx only

Eydenzelt®
(aflibercept-boav)
Injection

2 mg (0.05 mL of
40 mg/mL solution)

FOR INTRAVITREAL INJECTION

Each carton contains:

- one signle-dose vial of Eydenzelt (aflibercept-boav)
- one 18-gauge x 1½-inch, 5-micron, filter needle for withdrawal
  of the vial contents
- one 30-gauge x ½-inch injection needle for intravitreal injection
- one 1-mL syringe for administration
- one Prescribing Information

NDC 72606-026-02

CELLTRION USA
CELLTRION